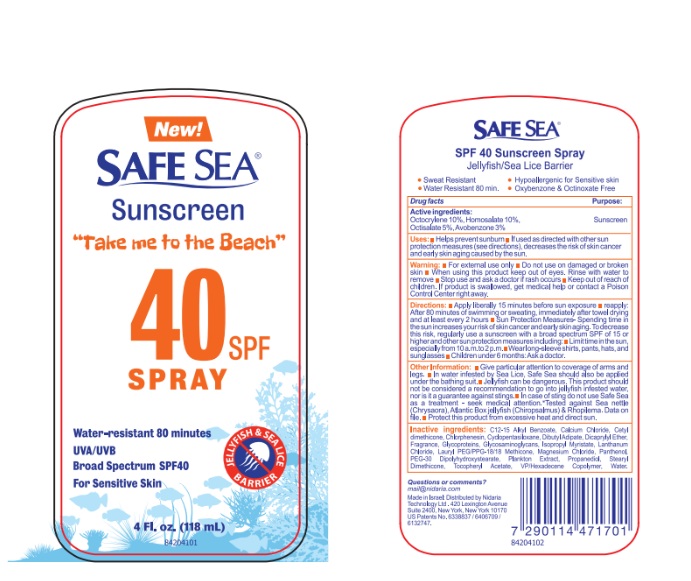 DRUG LABEL: Safe Sea SPF 40
NDC: 65435-0300 | Form: LIQUID
Manufacturer: NIDARIA TECHNOLOGY LTD
Category: otc | Type: HUMAN OTC DRUG LABEL
Date: 20251209

ACTIVE INGREDIENTS: OCTOCRYLENE 100 mg/1 mL; HOMOSALATE 100 mg/1 mL; OCTISALATE 50 mg/1 mL; AVOBENZONE 30 mg/1 mL
INACTIVE INGREDIENTS: STEARYL DIMETHICONE (400 MPA.S AT 50C); CETYL DIMETHICONE 25; VINYLPYRROLIDONE/HEXADECENE COPOLYMER; PANTHENOL; .ALPHA.-TOCOPHEROL ACETATE; LANTHANUM CHLORIDE; MAGNESIUM CHLORIDE; CALCIUM CHLORIDE; CHLORPHENESIN; PHAEODACTYLUM TRICORNUTUM; POLYSULFATED GLYCOSAMINOGLYCAN; LAURYL PEG/PPG-18/18 METHICONE; SACCHAROMYCES CEREVISIAE; PROPANEDIOL; WATER; DIBUTYL ADIPATE; ALKYL (C12-15) BENZOATE; CYCLOMETHICONE 5; DICAPRYLYL ETHER; PEG-30 DIPOLYHYDROXYSTEARATE; ISOPROPYL MYRISTATE

Safe Sea SPF 40

Active Ingredients Purpose

Octocrylene 10% Sunscreen

Homosalate 10% Sunscreen

Octisalate 5% Sunscreen

Avobenzone 3% Sunscreen

Uses

- Helps prevent sunburn
- If used as directed with other sun protection measures (see directions), decreases the risk of skin cancer and early skin aging caused by the sun.

Warning

- For external use only
- Do not use on damaged or broken skin
- When using this product keep out of eyes. Rinse with water to remove
- Stop use and ask a doctor if rash occurs.
- Keep out of reach of children. If product is swallowed, get medical help or contact a Poison Control Center right away.

Directions

- Apply liberally 15 minutes before sun exposure
- reapply: After 80 minutes of swimming or sweating, immediately after towel drying and at least every 2 hours
- Sun Protection Measures- Spending time in the sun increases your risk of skin cancer and early skin aging. To decrease this risk, regularly use a sunscreen with a broad spectrum SPF of 15 or higher and other sun protection measures including:
- Limit time in the sun, especially from 10 a.m.to 2 p.m.
- Wear long-sleeve shirts, pants, hats, and sunglasses
- Children under 6 months: Ask a doctor.

Other Information

- Give particular attention to coverage of arms and legs.
- In water infested by Sea Lice, Safe Sea should also be applied under the bathing suit.
- Jellyfish can be dangerous. This product should not be considered a recommendation to go into jellyfish infested water, nor is it a guarantee against stings.
- In case of sting do not use Safe Sea as a treatment - seek medical attention.*Tested against Sea nettle (Chrysaora), Atlantic Box jellyfish (Chiropsalmus) & Rhopilema. Data on file.
- Protect this product from excessive heat and direct sun.

Inactive ingredients

C12-15 Alkyl Benzoate, Calcium Chloride, Cetyl Dimethicone, Chlorphenesin, Cyclopentasiloxane, Dibutyl Adipate, Dicetyl Phthalate, Dimethicone, Fragrance, Glycoproteins, Glycosaminoglycans, Hydrogenated Castor Oil, Laureth-9, PEG/PPG-18/18 Methicone, Magnesium Chloride, Panthenol, PEG-30 Dipolyhydroxystearate, Plankton Extract, Propanediol, Stearyl Dimethicone, Tocopheryl Acetate, VP/Hexadecene Copolymer, Water.